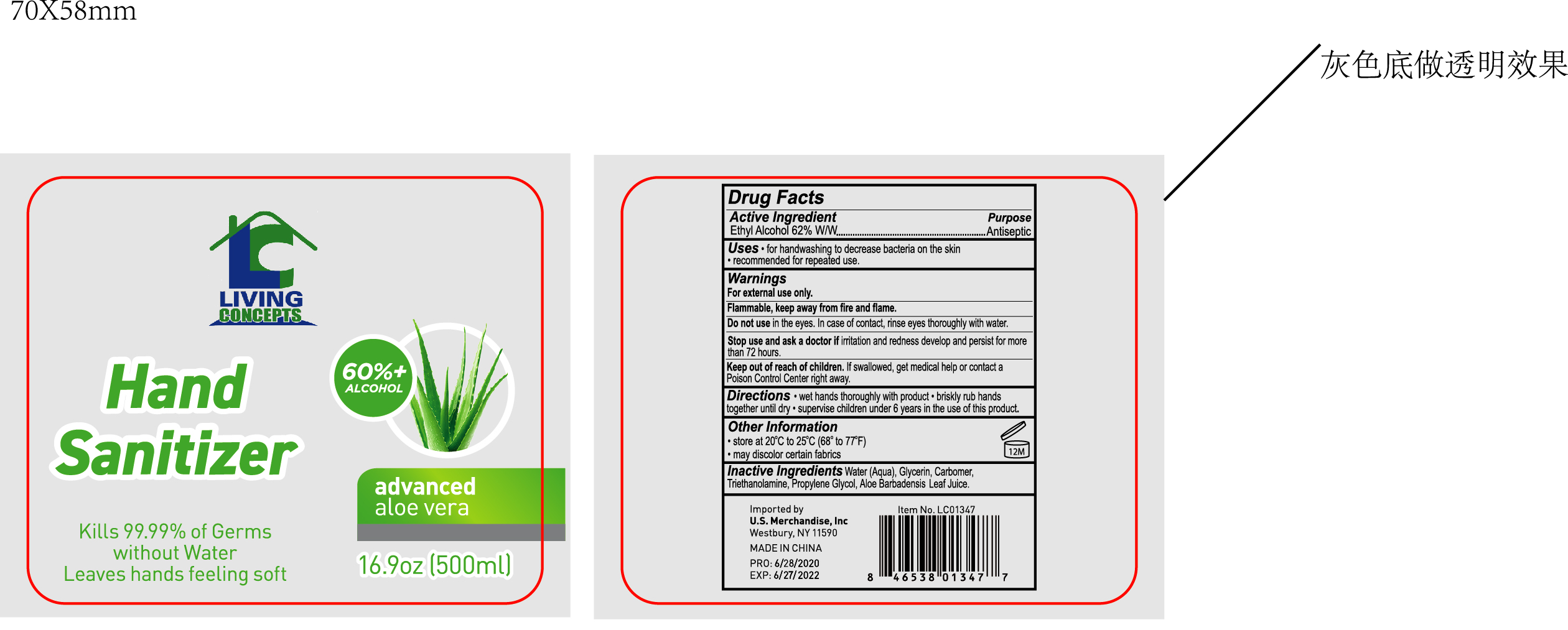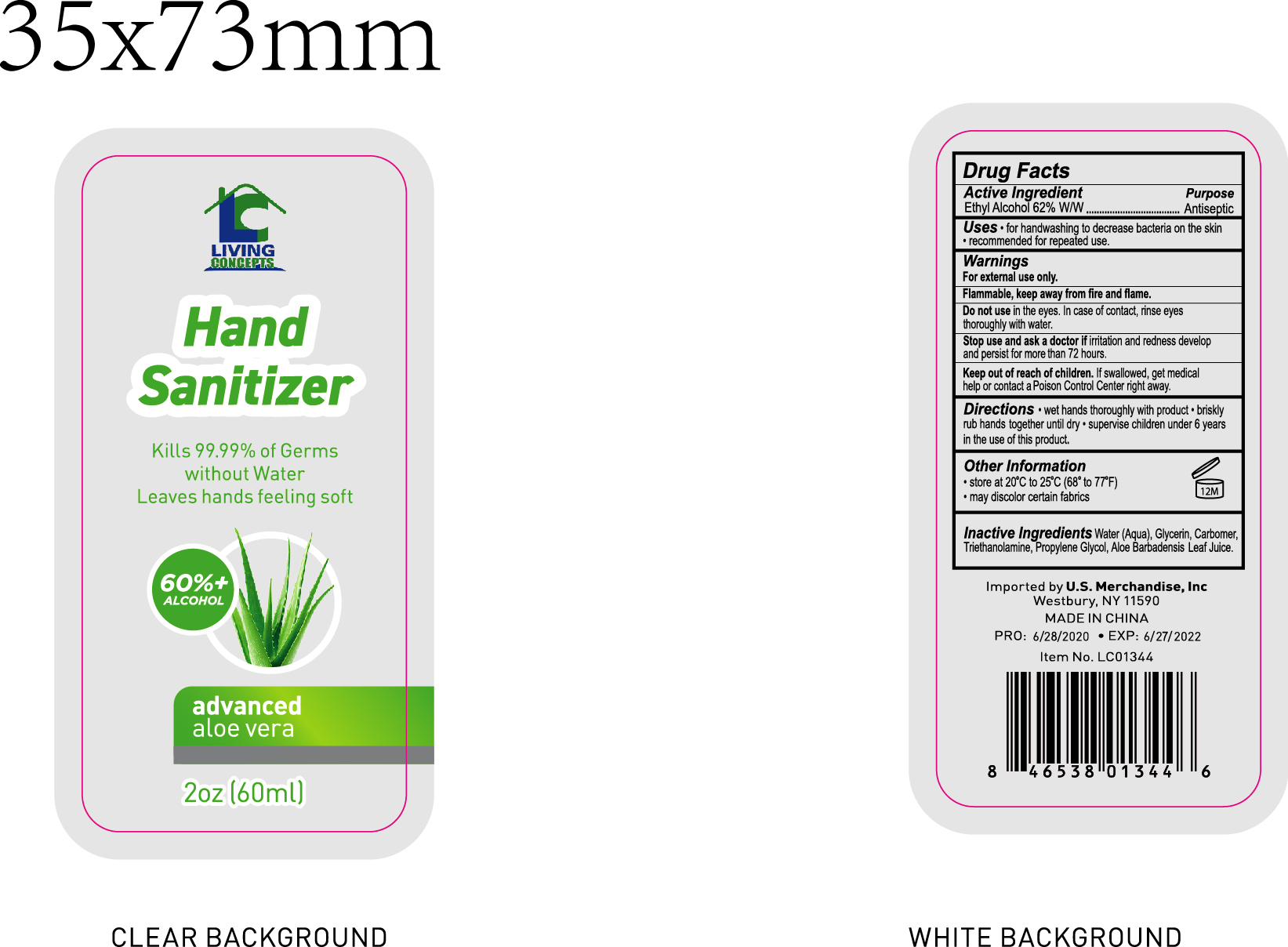 DRUG LABEL: HAND SANITIZER
NDC: 76681-002 | Form: GEL
Manufacturer: Taizhou Huangyan Delishi Daily Necessity Co., Ltd.
Category: otc | Type: HUMAN OTC DRUG LABEL
Date: 20200708

ACTIVE INGREDIENTS: ALCOHOL 62 mL/100 mL
INACTIVE INGREDIENTS: ALOE VERA LEAF; PROPYLENE GLYCOL; WATER; GLYCERIN; TRIETHANOLAMINE DODECYLBENZENESULFONATE; CARBOMER 934

HAND SANITIZER

Active Ingredient(s)

Ethyl Alcohol 62% v/v

Purpose

Antiseptic

Use

For handwashing to decrease bacteria on the skin.

Warnings

For external use only. Flammable. Keep away from fire and flame.

Do not use in the eyes. Incase of contact, rinse eyes thoroughly with water.

Stop use and ask a doctor if irritation or redness develops and persists for more than 72 hours.

Keep out of reach of children. If swallowed, get medical help or contact a Poison Control Center right away.

Do not use in the eyes. Incase of contact, rinse eyes thoroughly with water.

WHEN USING

For external use only. Flammable. Keep away from fire and flame.

Stop use and ask a doctor if irritation or redness develops and persists for more than 72 hours.

Keep out of reach of children. If swallowed, get medical help or contact a Poison Control Center right away.

Directions

Wet hands thoroughly with product. briskly rub hands together until dry.

Supervise children under 6 years in the use of this product.

Other information

Store at 20°C to 25°C (68°to 77°F)

May discolor certain fabrics.

Inactive ingredients

Water (Aqua), Glycerin, Carbomer, Triethanolamine, Propylene Glycol, Aloe Barbadensis Leaf Juice.

Package Label - Principal Display Panel

.